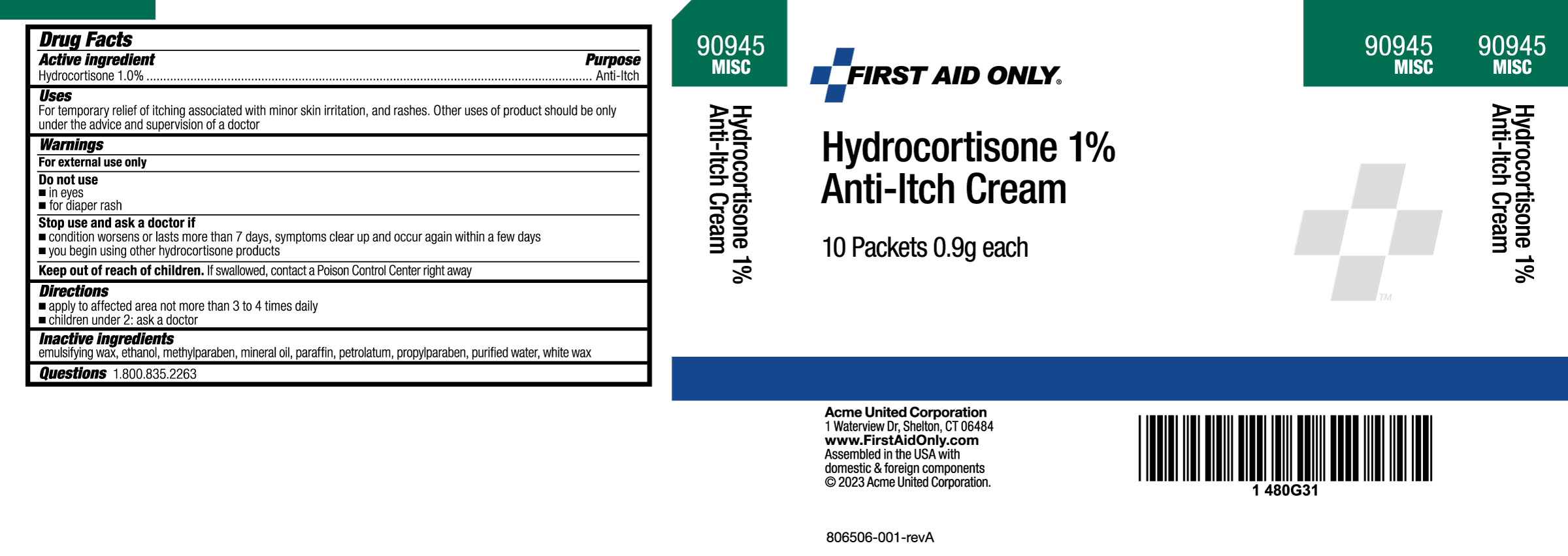 DRUG LABEL: Hydrocortisone
NDC: 0924-1133 | Form: CREAM
Manufacturer: Acme United Corporation
Category: otc | Type: HUMAN OTC DRUG LABEL
Date: 20241112

ACTIVE INGREDIENTS: HYDROCORTISONE 10 mg/1 g
INACTIVE INGREDIENTS: ALCOHOL; METHYLPARABEN; MINERAL OIL; PARAFFIN; PETROLATUM; PROPYLPARABEN; WATER; CETOSTEARYL ALCOHOL; POLYSORBATE 60; PEG-150 DISTEARATE; STEARETH-20

First Aid Only Hydrocortisone 1% Anti-Itch Cream

Drug Facts

Active Ingredient

Hydrocortisone 1.0%

Purpose

Anti-itch

Uses:

For temporary relief of itching associated with minor skin irritations and rashes.

Other uses of product should be only under the advice and supervision of a doctor

Warnings

For external use only

- Do not use
- in eyes
- for diaper rash

Stop use and ask a doctor if

▪ condition worsens or lasts for more than 7 days symptoms clear up and occur again within a few days

▪ you begin using other hydrocortisone products

KEEP OUT OF REACH OF CHILDREN.

If swallowed, contact a Poison Control Center right away.

Directions:

Adults and children over 2 years of age

- apply to affected area not more than 3 to 4 times daily
- children under 2, consult a doctor

Inactive ingredients

emulsifying wax, ethanol, methylparaben, mineral oil, paraffin, petrolatum, propylparaben, purified water, white wax

Questions

1.800.835.2263

Box Label